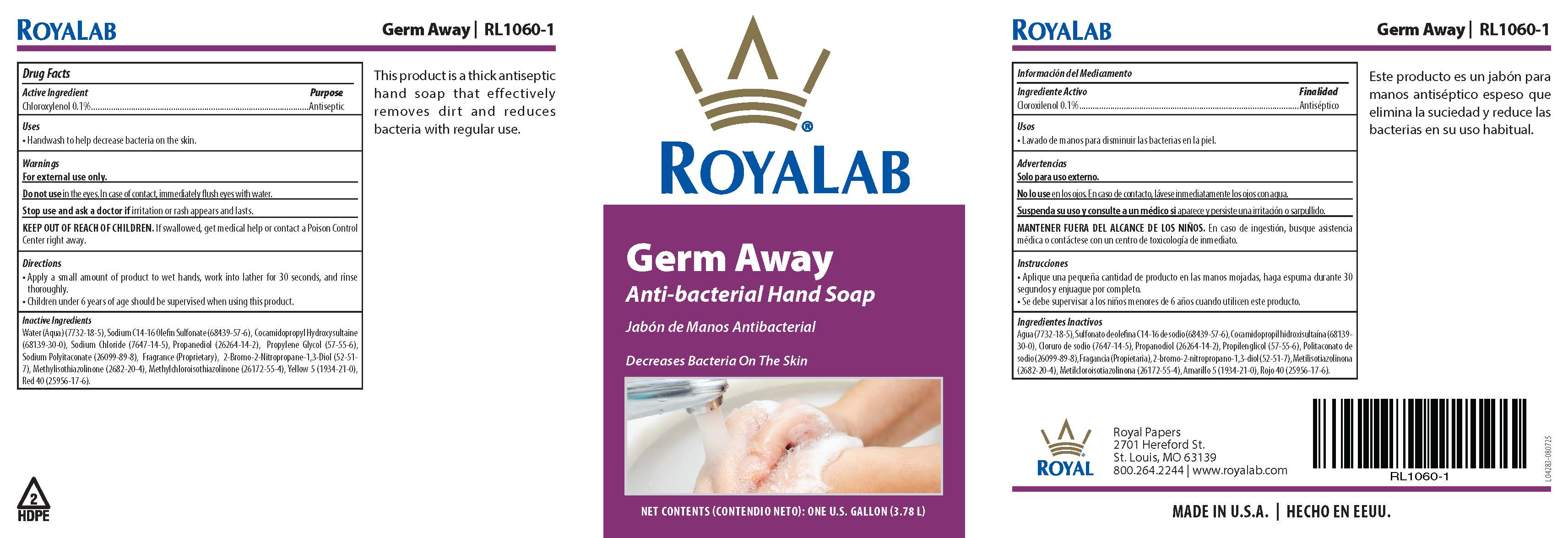 DRUG LABEL: RoyaLab Germ Away Antibacterial
NDC: 82077-701 | Form: SOAP
Manufacturer: Royal Papers, Inc.
Category: otc | Type: HUMAN OTC DRUG LABEL
Date: 20250807

ACTIVE INGREDIENTS: CHLOROXYLENOL 1 g/1 L
INACTIVE INGREDIENTS: BRONOPOL; COCAMIDOPROPYL HYDROXYSULTAINE; FD&C RED NO. 40; PROPANEDIOL; PROPYLENE GLYCOL; WATER; METHYLCHLOROISOTHIAZOLINONE; FD&C YELLOW NO. 5; SODIUM CHLORIDE; METHYLISOTHIAZOLINONE; SODIUM POLYITACONATE (2800 MW, PHOSPHATE TERMINATED); SODIUM C14-16 OLEFIN SULFONATE

Active Ingredient

Chloroxylenol 0.1%.

Purpose

Antiseptic

Uses

• Handwash to help decrease bacteria on the skin.

Warnings

For external use only.
Do not use in the eyes. In case of contact, immediately flush eyes with water.

Stop use and ask a doctor if irritation or rash appears and lasts.

KEEP OUT OF REACH OF CHILDREN. If swallowed, get medical help or contact a Poison Control Center right away.

Directions

• Apply a small amount of product to wet hands, work into lather for 30 seconds, and rinse thoroughly.
• Children under 6 years of age should be supervised when using this product.

Inactive Ingredients

Water (Aqua) (7732-18-5), Sodium C14-16 Olefin Sulfonate (68439-57-6), Cocamidopropyl Hydroxysultaine (68139-30-0), Sodium Chloride (7647-14-5), Propanediol (26264-14-2), Propylene Glycol (57-55-6), Sodium Polyitaconate (26099-89-8), Fragrance (Proprietary), 2-Bromo-2-Nitropropane-1,3-Diol (52-51-7), Methylisothiazolinone (2682-20-4), Methylchloroisothiazolinone (26172-55-4), Yellow 5 (1934-21-0), Red 40 (25956-17-6).